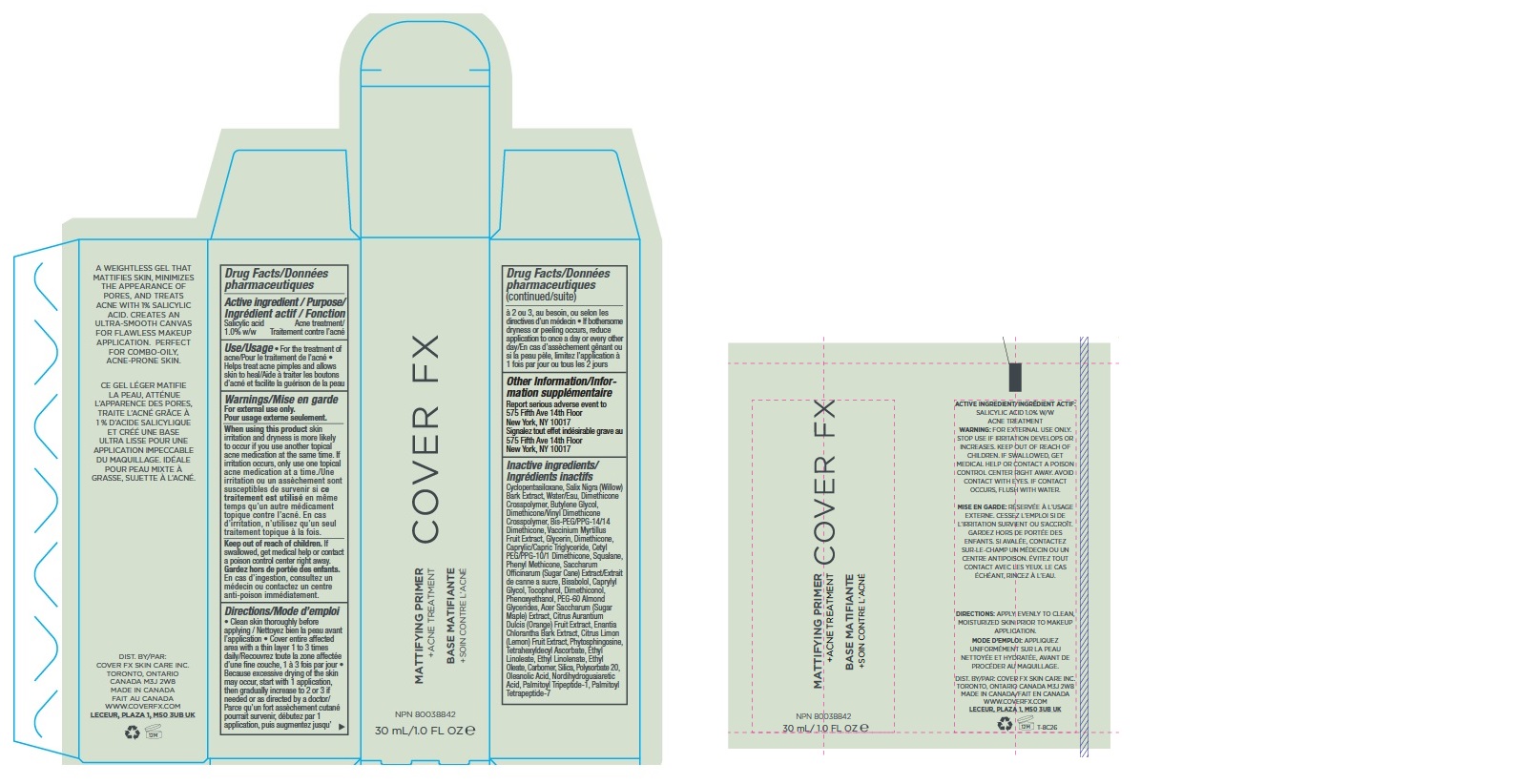 DRUG LABEL: Cover FX Mattifying Primer Plus Acne Treatment
NDC: 68327-073 | Form: GEL
Manufacturer: Cover FX Skin Care Inc
Category: otc | Type: HUMAN OTC DRUG LABEL
Date: 20181129

ACTIVE INGREDIENTS: SALICYLIC ACID 1 g/100 mL
INACTIVE INGREDIENTS: CYCLOMETHICONE 5; SALIX NIGRA BARK; WATER; BUTYLENE GLYCOL; DIMETHICONE/VINYL DIMETHICONE CROSSPOLYMER (SOFT PARTICLE); BIS-PEG/PPG-14/14 DIMETHICONE; BILBERRY; GLYCERIN; DIMETHICONE; MEDIUM-CHAIN TRIGLYCERIDES; CETYL PEG/PPG-10/1 DIMETHICONE (HLB 5); SQUALANE; PHENYL METHICONE (500 CST); SUGARCANE; .ALPHA.-BISABOLOL, (+)-; CAPRYLYL GLYCOL; TOCOPHEROL; DIMETHICONOL (40 CST); PHENOXYETHANOL; PEG-60 ALMOND GLYCERIDES; ACER SACCHARUM BARK/SAP; ORANGE; ANNICKIA CHLORANTHA BARK; LEMON; PHYTOSPHINGOSINE; TETRAHEXYLDECYL ASCORBATE; ETHYL LINOLEATE; ETHYL LINOLENATE; ETHYL OLEATE; CARBOMER HOMOPOLYMER TYPE C (ALLYL PENTAERYTHRITOL CROSSLINKED); SILICON DIOXIDE; POLYSORBATE 20; OLEANOLIC ACID; MASOPROCOL; PALMITOYL TRIPEPTIDE-1; PALMITOYL TETRAPEPTIDE-7

Cover FX Mattifying Primer Plus Acne Treatment

ACTIVE INGREDIENT

Salicylic Acid 1%

PURPOSE

Acne Treatment

USES

For the treatment of acne. Helps treat acne pimples and allows skin to heal.

WARNINGS

For external use only

When using this product

skin irritation and dryness is more likely to occur if you use another topical acne medication at the same time. If irritation occurs, only use one topical acne medication at a time.

Keep out of reach of children.

If swallowed, get medical help or contact a poison control center right away.

DIRECTIONS

- Clean skin thoroughly before applying.
- Cover entire affected area with a thin layer 1 to 3 times daily.
- Because excessive drying of the skin may occur, start with 1 application, then gradually increase to 2 or 3 if needed or as directed by a doctor.
- If bothersome dryness or peeling occurs, reduce application to once a day or every other day.

OTHER INFORMATION

Report serious adverse event to 575 Fifth Ave 14th Floor New York, NY 10017

INACTIVE INGREDIENTS

Cyclopentasiloxane, Salix Nigra (Willow) Bark Extract, Water/Eau, Dimethicone Crosspolymer, Butylene Glycol, Dimethicone/Vinyl Dimethicone Crosspolymer, Bis-PEG/PPG-14/14 Dimethicone, Vaccinium Myrtillus Fruit Extract, Glycerin, Dimethicone, Caprylic/Capric Triglyceride, Cetyl PEG/PPG-10/1 Dimethicone, Squalane, Phenyl Methicone, Saccharum Officinarum (Sugar Cane) Extract/Extrait de canne a sucre, Bisabolol, Caprylyl Glycol, Tocopherol, Dimethiconol, Phenoxyethanol, PEG-60 Almond Glycerides, Acer Saccharum (Sugar Maple) Extract, Citrus Aurantium Dulcis (Orange) Fruit Extract, Enantia Chlorantha Bark Extract, Citrus Limon (Lemon) Fruit Extract, Phytosphingosine, Tetrahexyldecyl Ascorbate, Ethyl Linoleate, Ethyl Linolenate, Ethyl Oleate, Carbomer, Silica, Polysorbate 20, Oleanolic Acid, Nordihydroguaiaretic Acid, Palmitoyl Tripeptide-1, Palmitoyl Tetrapeptide-7

COMPANY INFORMATION

Dist. By: Cover FX Skin Care Inc. Toronto Ontario Canada M3J 2W8
Made in Canada
www.coverfx.com

PRODUCT PACKAGING

COVER FX

MATTIFYING PRIMER +ACNE TREATMENT